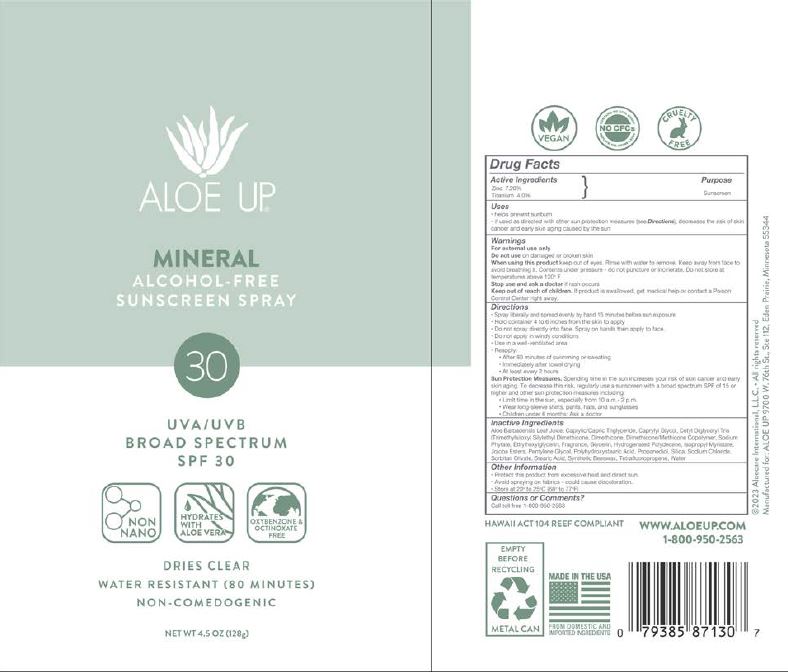 DRUG LABEL: Aloe UP SPF 30 Mineral
NDC: 61477-230 | Form: SPRAY
Manufacturer: Aloe Care International, LLC
Category: otc | Type: HUMAN OTC DRUG LABEL
Date: 20250618

ACTIVE INGREDIENTS: TITANIUM DIOXIDE 4 g/100 g; ZINC OXIDE 7.2 g/100 g
INACTIVE INGREDIENTS: ALOE BARBADENSIS LEAF JUICE; CAPRYLYL GLYCOL; CAPRYLIC/CAPRIC TRIGLYCERIDE; JOJOBA OIL, RANDOMIZED; DIMETHICONE; FRAGRANCE 13576; GLYCERIN; ISOPROPYL MYRISTATE; PENTYLENE GLYCOL; PROPANEDIOL; SILICON DIOXIDE; SODIUM CHLORIDE; SODIUM PHYTATE; SORBITAN OLIVATE; STEARIC ACID; SYNTHETIC BEESWAX; WATER; 2,3,3,3-TETRAFLUOROPROPENE; CETYL DIGLYCERYL TRIS(TRIMETHYLSILOXY)SILYLETHYL DIMETHICONE (950 MM2/S); ETHYLHEXYLGLYCERIN; C13-15 ALKANE; POLYHYDROXYSTEARIC ACID (2300 MW)

Aloe Up SPF 30 Mineral Spray

ACTIVE INGREDIENT

Zinc 7.20%

Titanium: 4.0%

PURPOSE

Sunscreen

INDICATIONS AND USAGE

- helps prevent sunburn
- if used as directed with other sun protection measures (see Directions), decreases the risk of skin cancer and early skin aging caused by the sun

WARNINGS

For external use only

Do not use on damaged or broken skin

When using this product keep out of eyes. Rinse with water to remove. Keep away from face to avoid breathing it. Contents under pressure - do not puncture or incinerate. Do not store at temperatured above 120°F

Stop use and ask a doctor if a rash occurs.

Keep out of reach of children. If product is swallowed, get medical help or contact a Poison Control Center right away.

DOSAGE AND ADMINISTRATION

- Spray liberally and spread evenly by hand 15 minutes before sun exposure.
- Hold container 4 to 6 inches from skin to apply
- Do not spray directly into face. Spray on hands then apply to face
- Do not apply in windy conditions
- Use in a well-ventilated area
- Reapply:
- After 80 minutes of swimming or sweating
- Immediately after towel drying
- At least every 2 hours
- Sun Protection Measures.Spending time in the sun increases your risk of skin cancer and early skin aging. To decrease this risk, regularly use a sunscreen with broad spectrum SPF of 15 or higher and other sun protection measures including:
- Limit time in the sun, especially from 10 am - 2 pm
- Wear long-sleeve shirts, pants, hats, and sunglasses
- Children under 6 months: Ask a doctor

OTHER SAFETY INFORMATION

- Protect this product from excessive heat and direct sun.
- Avoid spraying on fabrics - could cause discoloration
- Store at 20° to 25°C (68°F to 77°F)

INACTIVE INGREDIENT

Aloe Barbadensis Leaf Juice

C13-C15 Alkane

Caprylyl Glycol

Caprylic/Capric Triglyceride

Cetyl Diglyceryl Tris(Trimethylsiloxy)silylethyl Dimethicone

Dimethicone

Ethylhexylglycerin

Fragrance

Glycerin

Isopropyl Myristate

Jojoba Esters

Pentylene Glycol

Polyhydroxystearic Acid

Propanediol

Silica

Sodium Chloride

Sodium Phytate

Sorbitan Olivate

Stearic Acid

Synthetic Beeswax

Tetrafluoropropene

Water

QUESTIONS

Call toll free 1-800-950-2563